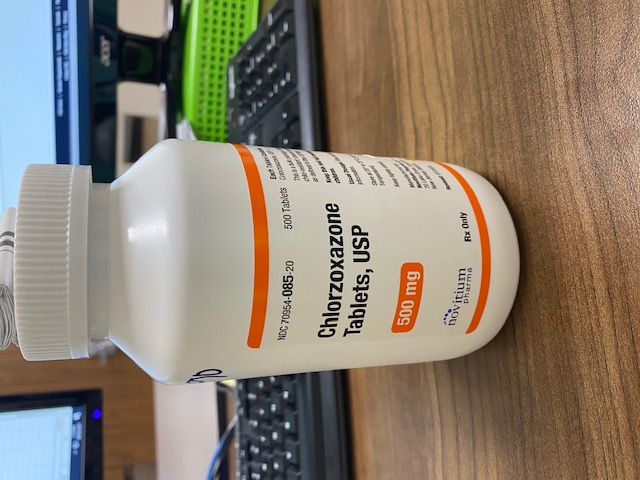 DRUG LABEL: CHLORZOXAZONE
NDC: 80175-0085 | Form: TABLET
Manufacturer: Central Packaging
Category: prescription | Type: HUMAN PRESCRIPTION DRUG LABEL
Date: 20210305

ACTIVE INGREDIENTS: CHLORZOXAZONE 500 mg/1 1

INDICATIONS AND USAGE

Chlorzoxazone is indicated as an adjunct to rest, physical therapy, and other measures for the relief of discomfort associated with acute, painful musculoskeletal conditions. The mode of action of this drug has not been clearly identified, but may be related to its sedative properties. Chlorzoxazone does not directly relax tense skeletal muscles in man.